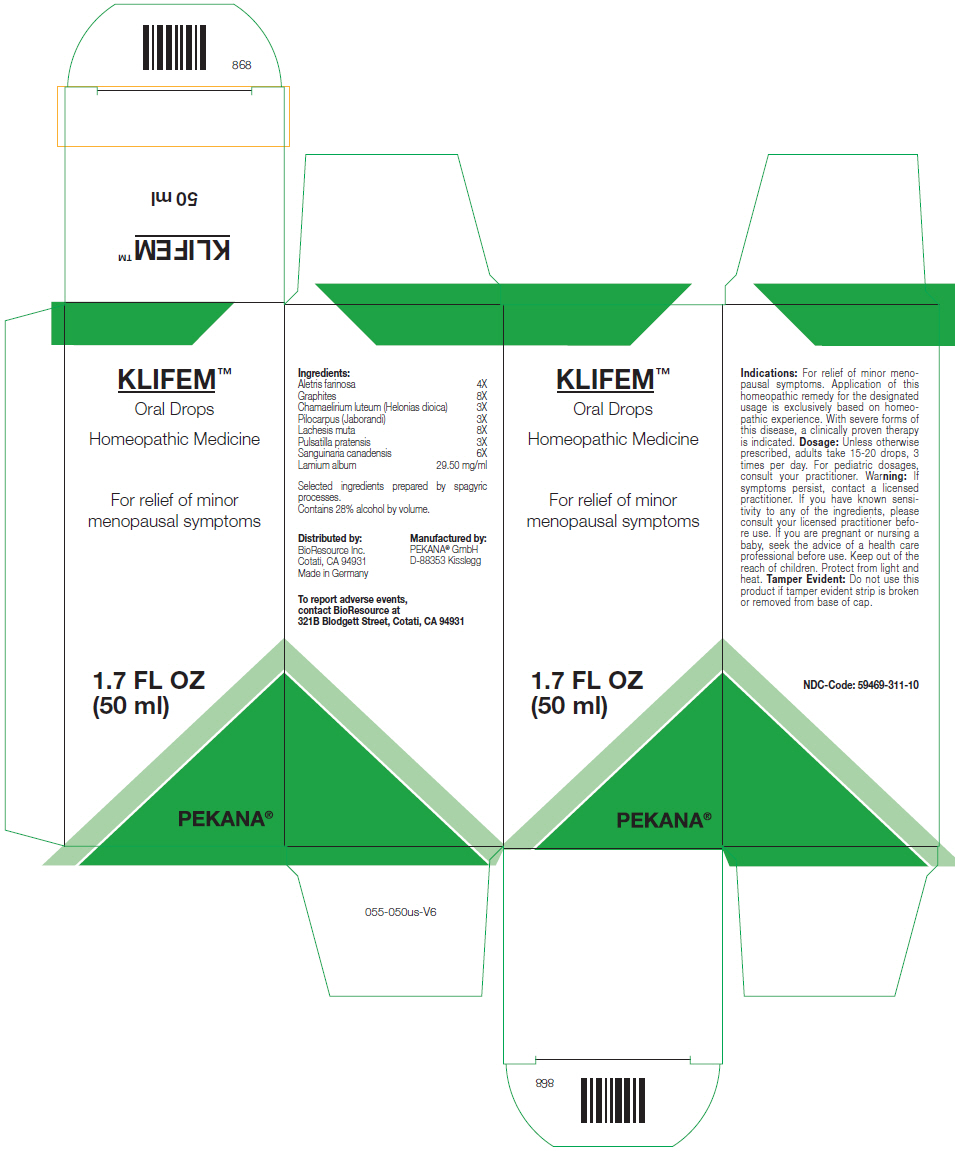 DRUG LABEL: KLIFEM
NDC: 59469-311 | Form: SOLUTION/ DROPS
Manufacturer: PEKANA Naturheilmittel GmbH
Category: homeopathic | Type: HUMAN OTC DRUG LABEL
Date: 20230111

ACTIVE INGREDIENTS: ALETRIS FARINOSA ROOT 4 [hp_X]/50 mL; GRAPHITE 8 [hp_X]/50 mL; CHAMAELIRIUM LUTEUM ROOT 3 [hp_X]/50 mL; PILOCARPUS JABORANDII LEAF 3 [hp_X]/50 mL; LACHESIS MUTA VENOM 8 [hp_X]/50 mL; PULSATILLA PRATENSIS FLOWERING TOP 3 [hp_X]/50 mL; SANGUINARIA CANADENSIS ROOT 6 [hp_X]/50 mL; LAMIUM ALBUM FLOWERING TOP 1475 mg/50 mL
INACTIVE INGREDIENTS: WATER; ALCOHOL

KLIFEM™

ACTIVE INGREDIENT

Ingredients:
Aletris farinosa | 4X
Graphites | 8X
Chamaelirium luteum (Helonias dioica) | 3X
Pilocarpus (Jaborandi) | 3X
Lachesis muta | 8X
Pulsatilla pratensis | 3X
Sanguinaria canadensis | 6X
Lamium album | 29.50 mg/ml

INACTIVE INGREDIENT

Selected ingredients prepared by spagyric processes.

Contains 28% alcohol by volume.

Indications

PURPOSE

For relief of minor menopausal symptoms. Application of this homeopathic remedy for the designated usage is exclusively based on homeopathic experience. With severe forms of this disease, a clinically proven therapy is indicated.

Dosage

Unless otherwise prescribed, adults take 15-20 drops, 3 times per day. For pediatric dosages, consult your practitioner.

Warning

If symptoms persist, contact a licensed practitioner. If you have known sensitivity to any of the ingredients, please consult your licensed practitioner before use. If you are pregnant or nursing a baby, seek the advice of a health care professional before use.

Keep out of the reach of children.

STORAGE AND HANDLING

Protect from light and heat.

Tamper Evident

Do not use this product if tamper evident strip is broken or removed from base of cap.

QUESTIONS

To report adverse events, contact BioResource at 321B Blodgett Street, Cotati, CA 94931

Distributed by:
BioResource Inc.
Cotati, CA 94931

Manufactured by:
PEKANA® GmbH
D-88353 Kisslegg

PRINCIPAL DISPLAY PANEL - 50 ml Bottle Box

KLIFEM™

Oral Drops

Homeopathic Medicine

For relief of minor
menopausal symptoms

1.7 FL OZ
(50 ml)

PEKANA®